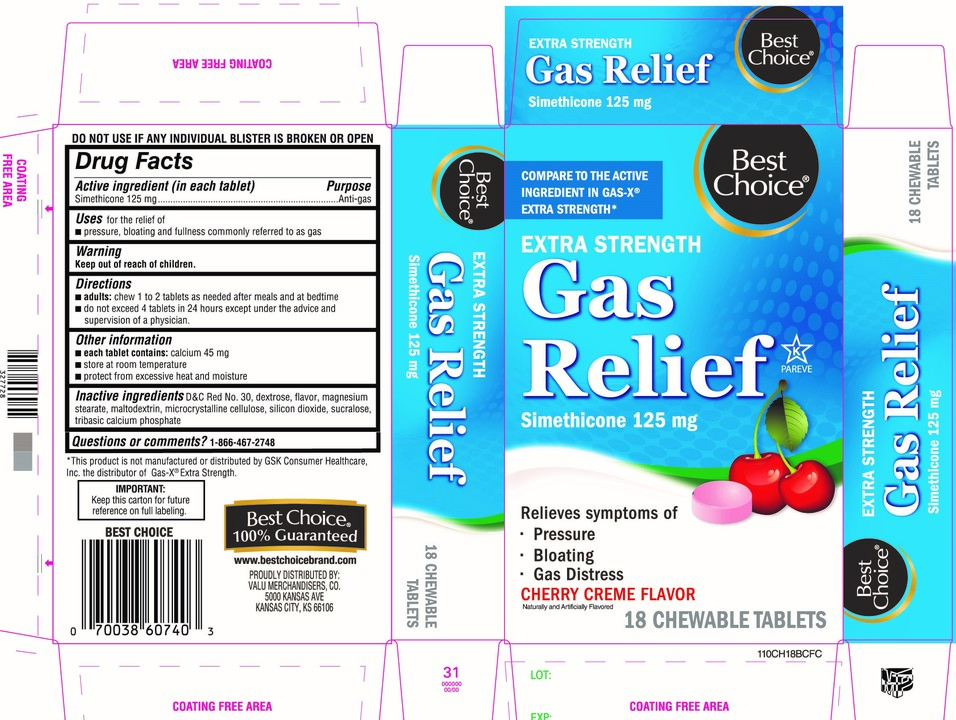 DRUG LABEL: Best Choice

NDC: 63941-110 | Form: TABLET, CHEWABLE
Manufacturer: BEST CHOICE (VALU MERCHANDISERS COMPANY)
Category: otc | Type: HUMAN OTC DRUG LABEL
Date: 20250716

ACTIVE INGREDIENTS: DIMETHICONE, UNSPECIFIED 125 mg/1 1
INACTIVE INGREDIENTS: D&C RED NO. 30; DEXTROSE, UNSPECIFIED FORM; MAGNESIUM STEARATE; MALTODEXTRIN; MICROCRYSTALLINE CELLULOSE; SILICON DIOXIDE; SUCRALOSE; TRIBASIC CALCIUM PHOSPHATE

Best Choice® Extra Strength Gas Relief

Active ingredient (in each tablet)

Simethicone 125 mg

Purpose

Anti-gas

Uses

For the relief of

- pressure, bloating and fullness commonly referred to as gas

Directions

- adults: chew 1 to 2 tablets as needed after meals and at bedtime.
- do not exceed 4 tablets in a 24 hours except under the advice and supervision of a physician.

Other information

- each tablets contains:calcium 45 mg
- store at room temperature
- protect from excessive heat and moisture

DO NOT USE IF ANY INDVIDUAL BLISTER IS BROKEN OR OPEN

Inactive ingredients

D&C Red No. 30, dextrose, flavor, magnesium stearate, maltodextrin, microcrystalline cellulose, silicon dioxide, sucralose, tribasic calcium phosphate.

Principal Display Panel

Best Choice®

NDC 63941-110-18

*COMPARE TO THE ACTIVE INGREDIENT IN GAS-X®EXTRA STRENGTH

EXTRA STRENGTH

Gas Relief

Simethicone 125 mg

Relieves symptoms of:

- Pressure
- Bloating
- Gas Distress

CHERRY CREME FLAVOR

NATURALLY AND ARTIFICIALLY FLAVORED

18 CHEWABLE TABLETS

K PAREVE

*This product is not manufactured or distributed by GSK Consumer Healthcare, Inc. the distributor of Gas-X®Extra strength.

Best Choice®100% Guaranteed

www.bestchoicebrand.com

PROUDLY DISTRIBUTED BY:

VALU MERCHANDISERS, CO.

5000 KANSAS AVE, KANSAS CITY, KS 66106

IMPORTANT:Keep this carton for future reference on full labeling.